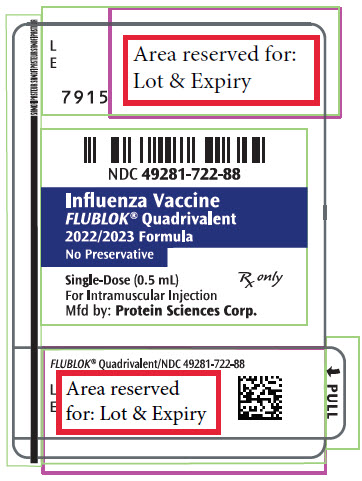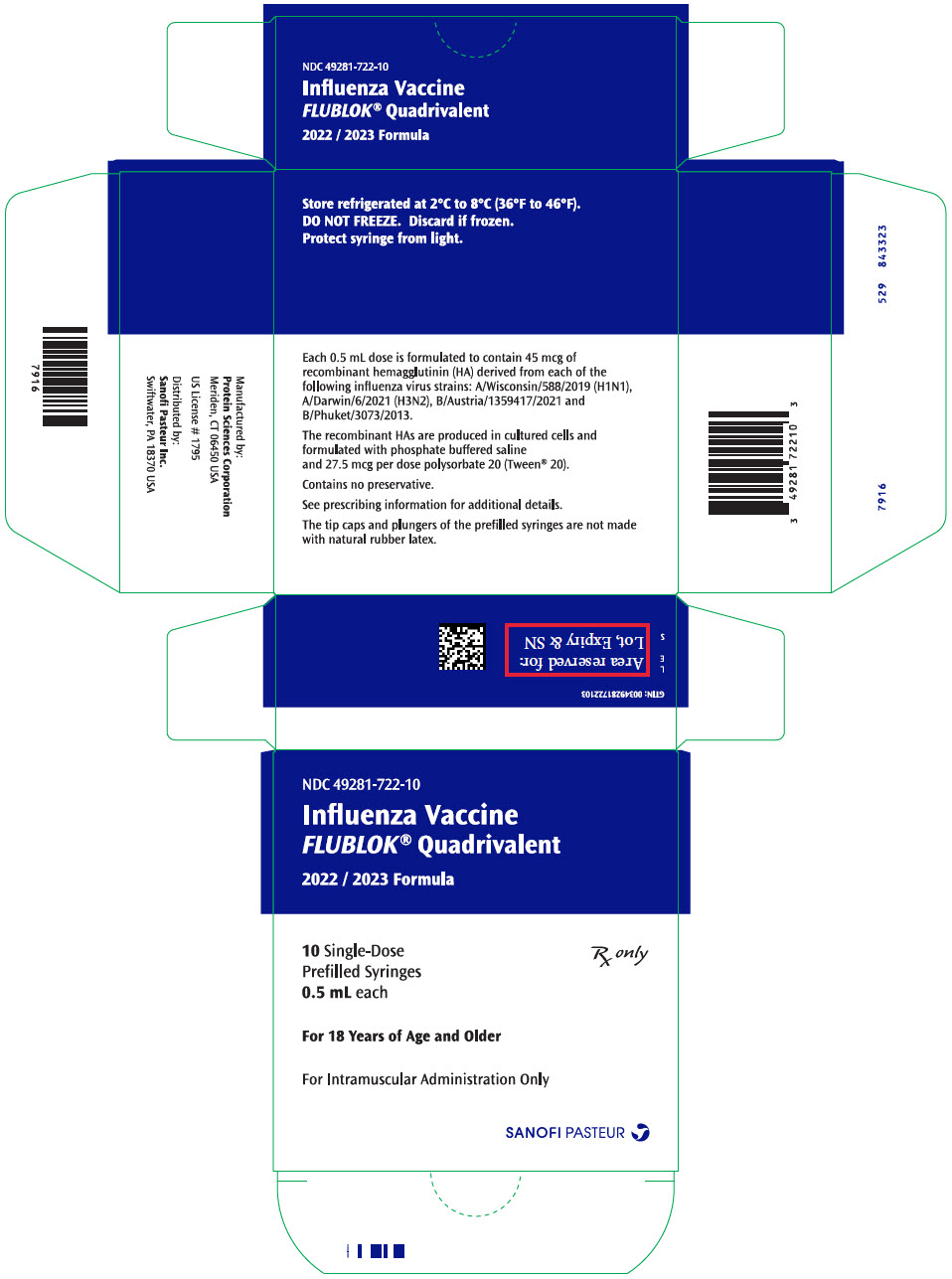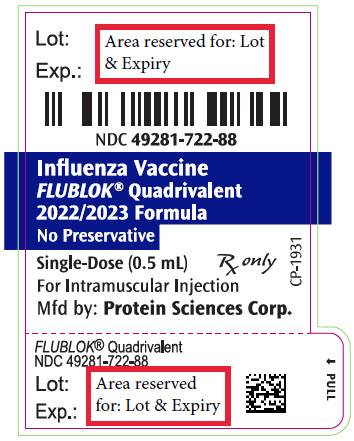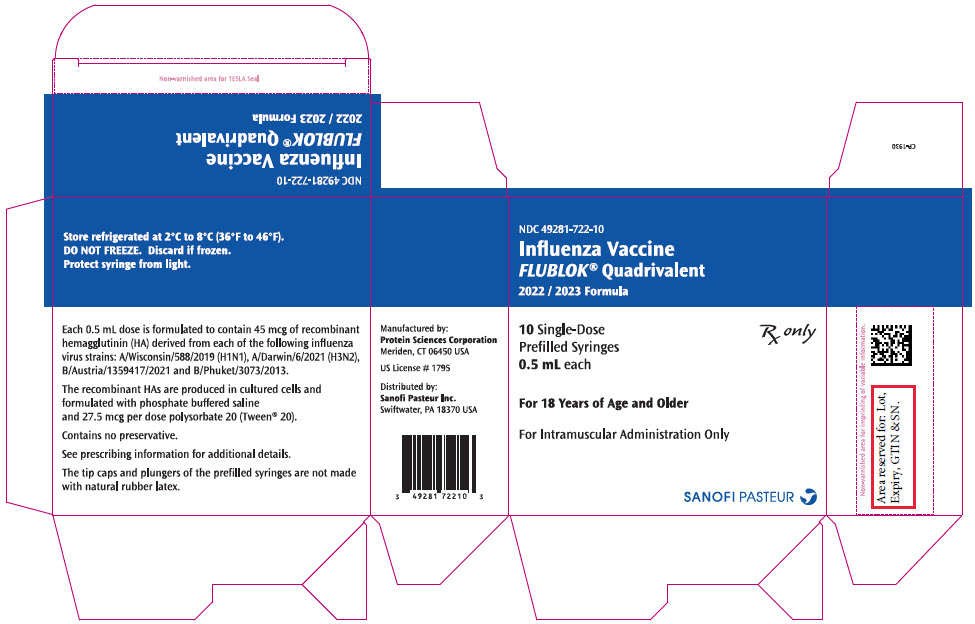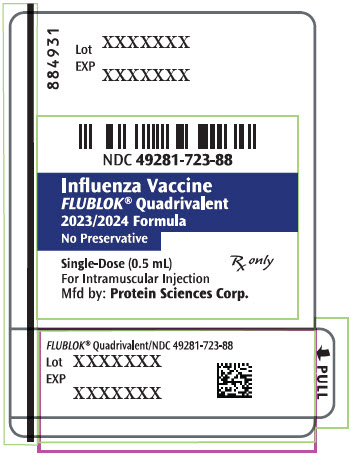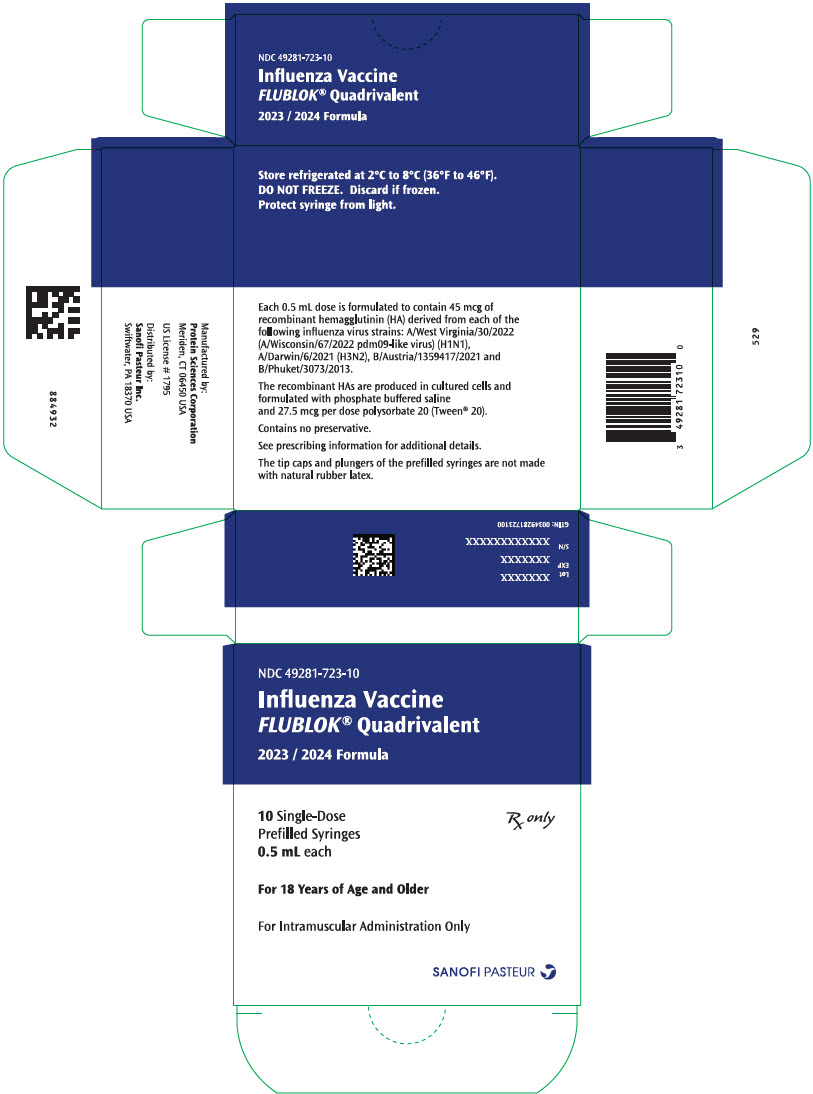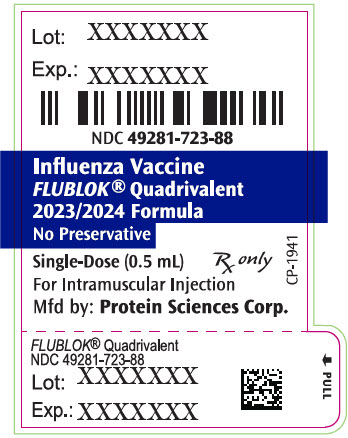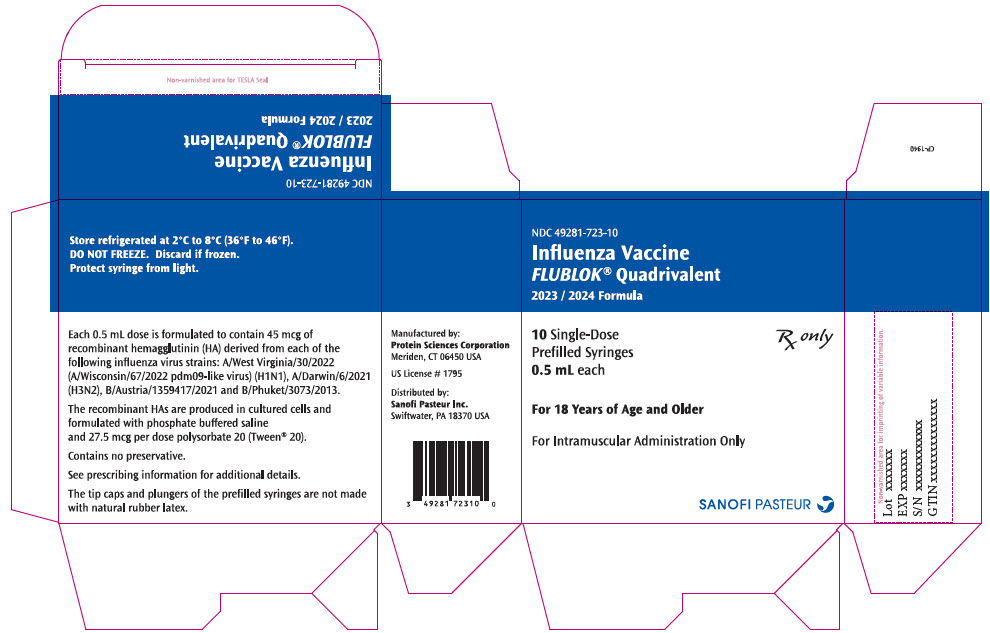 DRUG LABEL: Flublok Quadrivalent Northern Hemisphere
NDC: 49281-722 | Form: INJECTION
Manufacturer: Sanofi Pasteur Inc.
Category: other | Type: VACCINE LABEL
Date: 20220926

ACTIVE INGREDIENTS: INFLUENZA A VIRUS A/WISCONSIN/588/2019 (H1N1) RECOMBINANT HEMAGGLUTININ ANTIGEN 45 ug/0.5 mL; INFLUENZA A VIRUS A/DARWIN/6/2021 (H3N2) RECOMBINANT HEMAGGLUTININ ANTIGEN 45 ug/0.5 mL; INFLUENZA B VIRUS B/AUSTRIA/1359417/2021 RECOMBINANT HEMAGGLUTININ ANTIGEN 45 ug/0.5 mL; INFLUENZA B VIRUS B/PHUKET/3073/2013 RECOMBINANT HEMAGGLUTININ ANTIGEN 45 ug/0.5 mL
INACTIVE INGREDIENTS: SODIUM PHOSPHATE, MONOBASIC, MONOHYDRATE; SODIUM PHOSPHATE, DIBASIC, DODECAHYDRATE; SODIUM CHLORIDE; POLYSORBATE 20; OCTOXYNOL-9; WATER

HIGHLIGHTS OF PRESCRIBING INFORMATION

These highlights do not include all the information needed to use Flublok® Quadrivalent safely and effectively. See full prescribing information for Flublok Quadrivalent.
Flublok Quadrivalent (Influenza Vaccine), Sterile Solution for Intramuscular Injection
2023-2024 Formula
Initial U.S. Approval: 2013

1 INDICATIONS AND USAGE

- Flublok Quadrivalent is a vaccine indicated for active immunization against disease caused by influenza A subtype viruses and influenza type B viruses contained in the vaccine. Flublok Quadrivalent is approved for use in persons 18 years of age and older. (1)

2 DOSAGE AND ADMINISTRATION

For intramuscular (IM) injection only (0.5 mL). (2)

3 DOSAGE FORMS AND STRENGTHS

A sterile solution for injection supplied in 0.5 mL single dose prefilled syringes. (3)

4 CONTRAINDICATIONS

- Severe allergic reaction (e.g., anaphylaxis) to any component of the vaccine. (4, 6.2, 11)

5 WARNINGS AND PRECAUTIONS

- Appropriate medical treatment and supervision must be available to manage possible anaphylactic reactions following administration of Flublok Quadrivalent. (5.1)
- If Guillain Barré syndrome has occurred within 6 weeks of receipt of a prior influenza vaccine, the decision to give Flublok Quadrivalent should be based on careful consideration of potential benefits and risks. (5.2)

6 ADVERSE REACTIONS

- In adults 18 through 49 years of age, the most common (≥10%) injection-site reactions were tenderness (48%) and pain (37%); the most common (≥10%) solicited systemic adverse reactions were headache (20%), fatigue (17%), myalgia (13%) and arthralgia (10%). (6.1)
- In adults 50 years of age and older, the most common (≥10%) injection site reactions were tenderness (34%) and pain (19%); the most common (≥10%) solicited systemic adverse reactions were headache (13%) and fatigue (12%). (6.1)

To report SUSPECTED ADVERSE REACTIONS, contact Sanofi Pasteur Inc., at 1-800-822-2463 (1-800-Vaccine) or VAERS at 1-800-822-7967 or www.vaers.hhs.gov.

8 USE IN SPECIFIC POPULATIONS

- Pregnancy: Pregnancy outcomes in women exposed to Flublok Quadrivalent during pregnancy are being monitored. Contact: Sanofi Pasteur Inc. by calling 1-800-822-2463. (8.1)

FULL PRESCRIBING INFORMATION

1 INDICATIONS AND USAGE

Flublok Quadrivalent is a vaccine indicated for active immunization against disease caused by influenza A subtype viruses and type B viruses contained in the vaccine. Flublok Quadrivalent is approved for use in persons 18 years of age and older [see Clinical Studies (14)].

2 DOSAGE AND ADMINISTRATION

For intramuscular injection only.

2.1 Dosage

Administer Flublok Quadrivalent as a single 0.5 mL dose.

2.2 Administration

Invert the prefilled syringe containing Flublok Quadrivalent gently prior to affixing the appropriate size needle for intramuscular administration.

Parenteral drug products should be inspected visually for particulate matter and discoloration prior to administration whenever solution and container permit. If either of these conditions exists, the vaccine should not be administered.

The preferred site for injection is the deltoid muscle. Flublok Quadrivalent should not be mixed in the same syringe with any other vaccine.

3 DOSAGE FORMS AND STRENGTHS

Flublok Quadrivalent is a sterile solution supplied in prefilled, single-dose syringes, 0.5 mL.

4 CONTRAINDICATIONS

Flublok Quadrivalent is contraindicated in individuals with known severe allergic reactions (e.g., anaphylaxis) to any component of the vaccine [see Postmarketing Experience (6.2) and Description (11)].

5 WARNINGS AND PRECAUTIONS

5.1 Managing Allergic Reactions

Appropriate medical treatment and supervision must be available to manage possible anaphylactic reactions following administration of the vaccine.

5.2 Guillain Barré Syndrome

The 1976 swine influenza vaccine was associated with an increased frequency of Guillain-Barré Syndrome (GBS). Evidence for a causal relation of GBS with other influenza vaccines is inconclusive; if an excess risk exists, it is probably slightly more than one additional case per 1 million persons vaccinated. If GBS has occurred within 6 weeks of receipt of a prior influenza vaccine, the decision to give Flublok should be based on careful consideration of the potential benefits and risks.

5.3 Altered Immunocompetence

If Flublok Quadrivalent is administered to immunocompromised individuals, including persons receiving immunosuppressive therapy, the immune response may be diminished.

5.4 Limitations of Vaccine Effectiveness

Vaccination with Flublok Quadrivalent may not protect all vaccine recipients.

6 ADVERSE REACTIONS

In adults 18 through 49 years of age, the most common (≥10%) injection-site reactions were tenderness (48%) and pain (37%); the most common (≥10%) solicited systemic adverse reactions were headache (20%), fatigue (17%), myalgia (13%), and arthralgia (10%) [see Clinical Trials Experience (6.1)].

In adults 50 years of age and older, the most common (≥10%) injection site reactions were tenderness (34%) and pain (19%); the most common (≥10%) solicited systemic adverse reactions were headache (13%) and fatigue (12%) [see Clinical Trials Experience (6.1)].

6.1 Clinical Trials Experience

Because clinical studies are conducted under widely varying conditions, adverse reaction rates observed in the clinical studies of a vaccine cannot be directly compared to rates in the clinical studies of another vaccine and may not reflect the rates observed in clinical practice.

Flublok Quadrivalent

Flublok Quadrivalent has been administered to and safety data collected from 998 adults 18-49 years of age (Study 1) and 4328 adults 50 years of age and older (Study 2).

In Studies 1 and 2, local (injection site) and systemic adverse reactions were solicited with the use of a memory aid for 7 days following vaccination, unsolicited adverse events were collected for ~28 days post-vaccination, and serious adverse events (SAEs) were collected for 6 months post-vaccination via clinic visit or remote contact.

Study 1 included 1330 subjects 18 through 49 years of age for safety analysis, randomized to receive Flublok Quadrivalent (n=998) or a comparator inactivated influenza vaccine (Fluarix® Quadrivalent, manufactured by GlaxoSmithKline) (n=332) [see Clinical Studies (14)]. The mean age of participants was 33.5 years. Overall, 65% of subjects were female, 59% white/Caucasian, 37% black/African American, 1.0% Native Hawaiian/Pacific Islander, 0.8% American Indian/Alaskan Native, 0.5% Asian, 1.4% other racial groups, and 16% of Hispanic/Latino ethnicity. Table 1 summarizes the incidence of solicited local and systemic adverse reactions reported within seven days of vaccination with Flublok Quadrivalent or the comparator vaccine.

Table 1: Frequency of Solicited Local Injection Site Reactions and Systemic Adverse Reactions within 7 Days of Administration of Flublok Quadrivalent or Comparator [Comparator = U.S.–licensed comparator quadrivalent inactivated influenza vaccine manufactured by GlaxoSmithKline.] in Adults 18-49 Years of Age, Study 1 (Reactogenicity Populations), [Study 1 is registered as NCT02290509 under the National Clinical Trials registry.]
Reactogenicity Term | Flublok Quadrivalent N=996 % |  |  | Comparator N=332 %
Reactogenicity Term | Any Grade [Denominators for fever: Flublok Quadrivalent n = 990, Comparator n = 327.] | Grade 3 | Grade 4 | Any Grade | Grade 3 | Grade 4
Subjects with ≥1 injection site reaction [Reactogenicity Populations were defined as all randomized subjects who received study vaccine according to the treatment actually received and who had at least one non-missing data point for injection site, systemic or body temperature reactogenicity categories. For local pain, tenderness and systemic reactions: Grade 1 = No interference with activities. Grade 2 = Prevented some activities, and headache may have required non-narcotic pain reliever. Grade 3 = Prevented most or all normal activities or required prescription medications. Grade 4 = Required visit to ER or hospitalization. For injection site redness and firmness/swelling: Grade 1=25 to ≤50 mm (small). Grade 2=51 to ≤100 mm (medium). Grade 3=>100 mm (large). Grade 4=necrosis or exfoliative dermatitis.] , [Denominators for injection site reactions: Flublok Quadrivalent n = 996, Comparator n =332.] | 51 | 1 | 0 | 52 | 2 | 0
Local Tenderness | 48 | 1 | 0 | 47 | 1 | 0
Local Pain | 37 | 1 | 0 | 36 | 1 | 0
Firmness / Swelling | 5 | 0 | 0 | 3 | 0 | 0
Redness | 4 | 0 | 0 | 1 | 0 | 0
Subjects with ≥1 systemic reaction, [Denominators for systemic reactions: Flublok Quadrivalent n = 994, Comparator n = 332.] | 34 | 2 | <1 | 36 | 3 | <1
Headache | 20 | 1 | 0 | 21 | 2 | <1
Fatigue | 17 | 1 | 0 | 17 | 1 | 0
Muscle Pain | 13 | 1 | 0 | 12 | 1 | 0
Joint Pain | 10 | 1 | 0 | 10 | 1 | 0
Nausea | 9 | 1 | <1 | 9 | 1 | 0
Shivering / Chills | 7 | 1 | 0 | 6 | 1 | 0
Fever, [Fever defined as ≥100.4°F (38°C). Grade 1 (≥100.4°F to ≤101.1°F); Grade 2 (101.2°F to ≤102.0°F); Grade 3 (102.1°F to ≤104°F). Grade 4 >104°F.] | 2 | <1 | 0 | 1 | <1 | 0
NOTE: Data based on the most severe response reported by subjects. Results ≥1% reported to nearest whole percent; results >0 but <1% reported as <1%.

Study 2 included 8672 subjects 50 years of age and older for safety analysis, randomized to receive Flublok Quadrivalent (n=4328) or Comparator (Fluarix Quadrivalent, manufactured by GlaxoSmithKline) as an active control (n=4344) [see Clinical Studies (14)]. The mean age of participants was 62.7 years. Overall, 58% of subjects were female, 80% white/Caucasian, 18% black/African American, 0.9% American Indian/Alaskan Native, 0.4% Asian, 0.2% Native Hawaiian/Pacific Islander, 0.7% other racial groups, and 5% of Hispanic/Latino ethnicity. Table 2 summarizes the incidence of solicited local and systemic adverse reactions reported within seven days of vaccination with Flublok Quadrivalent or Comparator.

Table 2: Frequency of Solicited Local Injection Site Reactions and Systemic Adverse Reactions within 7 Days of Administration of Flublok Quadrivalent or Comparator [Comparator = U.S.–licensed comparator quadrivalent inactivated influenza vaccine, Fluarix Quadrivalent, manufactured by GlaxoSmithKline.] in Adults 50 Years of Age and Older, Study 2 (Reactogenicity Populations) [Study 2 is registered as NCT02285998 under the National Clinical Trials registry.] , [Reactogenicity Populations were defined as all randomized subjects who received study vaccine according to the treatment actually received and who had at least one non-missing data point for injection site, systemic or body temperature reactogenicity categories. For local pain, tenderness, and systemic reactions: Grade 1=No interference with activity. Grade 2=Some interference with activity. Grade 3=Prevents daily activity. Grade 4=Required ER visit or hospitalization. For injection site redness and firmness/swelling: Grade 1=25 to ≤50 mm (small). Grade 2=51 to ≤100 mm (medium). Grade 3=>100 mm (large). Grade 4=necrosis or exfoliative dermatitis.]
Reactogenicity Term | Flublok Quadrivalent N=4312 % |  |  | Comparator N=4327 %
Reactogenicity Term | Any Grade | Grade 3 | Grade 4 | Any Grade | Grade 3 | Grade 4
Subjects with ≥1 injection site reaction, [Denominators for injection site reactions: Flublok Quadrivalent n = 4307, Comparator n = 4319.] | 38 | <1 | <1 | 40 | <1 | <1
Local Tenderness | 34 | <1 | <1 | 37 | <1 | <1
Local Pain | 19 | <1 | 0 | 22 | <1 | <1
Firmness / Swelling | 3 | <1 | 0 | 3 | <1 | 0
Redness | 3 | <1 | 0 | 2 | <1 | 0
Subjects with ≥1 systemic reactogenicity event, [Denominators for systemic reactions: Flublok Quadrivalent n = 4306, Comparator n = 4318.] | 25 | 1 | <1 | 26 | 1 | <1
Headache | 13 | <1 | <1 | 14 | 1 | <1
Fatigue | 12 | <1 | 0 | 12 | <1 | <1
Muscle Pain | 9 | <1 | <1 | 9 | <1 | <1
Joint Pain | 8 | <1 | 0 | 8 | <1 | <1
Nausea | 5 | <1 | 0 | 5 | <1 | <1
Shivering / Chills | 5 | <1 | 0 | 4 | <1 | <1
Fever [Denominators for fever: Flublok Quadrivalent n = 4262, Comparator n = 4282.] , [Fever defined as ≥100.4°F (38°C). Grade 1 (≥100.4°F to ≤101.1°F); Grade 2 (101.2°F to ≤102.0°F); Grade 3 (102.1°F to ≤104°F). Grade 4 >104°F.] | <1 | <1 | 0 | 1 | <1 | 0
NOTE: Data based on the most severe response reported by subjects. Results ≥1% reported to nearest whole percent; results >0 but <1% reported as <1%.

Among adults 18-49 years of age (Study 1), through 6 months post-vaccination, no deaths were reported. SAEs were reported by 12 subjects, 10 (1%) Flublok Quadrivalent recipients and 2 (0.6%) Comparator recipients. No SAEs were considered related to study vaccine.

Among adults 50 years of age and older (Study 2), 20 deaths occurred in the 6 months post-vaccination, including 8 Flublok Quadrivalent and 12 Comparator recipients. No deaths were considered related to study vaccine. SAEs were reported by 145 (3.4%) Flublok Quadrivalent recipients and 132 (3%) Comparator recipients. No SAEs were considered related to study vaccine.

In the 28 days following vaccination, one or more unsolicited treatment emergent adverse events occurred in 10.3% of Flublok Quadrivalent and 10.5% of Comparator recipients in Study 1 (adults 18-49 years of age) and in 13.9% of Flublok Quadrivalent and 14.1% of Comparator recipients in Study 2 (adults ≥50 years of age). In both studies, rates of individual events were similar between treatment groups, and most events were mild to moderate in severity.

Flublok (Trivalent Formulation)

The safety experience with Flublok is relevant to Flublok Quadrivalent because both vaccines are manufactured using the same process and have overlapping compositions [see Description (11)].

Flublok (trivalent formulation) has been administered to and safety data collected from a total of 4547 subjects in five clinical trials (Studies 3-7): 2497 adults 18 through 49 years, 972 adults 50 through 64 years, and 1078 adults 65 years and older. In Studies 3 - 5 and 7, SAEs were collected for 6 months post-vaccination. Study 6 collected SAEs through 30 days following receipt of vaccine. Study 6 also actively solicited pre-specified common hypersensitivity-type reactions through 30 days following receipt of vaccine as a primary endpoint.

Study 3 included 4648 subjects 18 through 49 years of age for safety analysis, randomized to receive Flublok (n=2344) or placebo (n=2304) [see Clinical Studies (14)].

Study 4 included 602 subjects 50 through 64 years of age for safety analysis, randomized to receive Flublok (n=300) or another U.S.–licensed trivalent influenza vaccine (Fluzone®, manufactured by Sanofi Pasteur, Inc.) as an active control (n=302).

Study 5 included 869 subjects aged 65 years and older for safety analysis, randomized to receive Flublok (n=436) or another U.S.–licensed trivalent influenza vaccine (Fluzone) as an active control (n=433).

Study 6 included 2627 subjects aged 50 years and older for safety analysis, randomized to receive Flublok (n=1314) or another U.S.–licensed trivalent influenza vaccine (Afluria, manufactured by Seqirus Pty Ltd.) as an active control (n=1313). Among subjects 50 through 64 years of age, 672 received Flublok and 665 received Afluria. Among subjects aged 65 years and older, 642 received Flublok and 648 received Afluria.

Study 7 was a Phase 2 dose-finding trial conducted in adults 18 through 49 years of age, 153 of whom received Flublok 135 mcg, the licensed trivalent formulation.

Serious Adverse Events

Among 2497 adults 18-49 years of age (Studies 3 and 7 pooled), through 6 months post-vaccination, two deaths were reported, one in a Flublok recipient and one in a placebo recipient. Both deaths occurred more than 28 days following vaccination and neither was considered vaccine-related. SAEs were reported by 32 Flublok recipients and 35 placebo recipients. One SAE (pleuropericarditis) in a Flublok recipient was assessed as possibly related to the vaccine.

Among 972 adults 50-64 years of age (Studies 4 and 6 pooled), through up to 6 months post-vaccination, no deaths occurred, and SAEs were reported by 10 subjects, 6 Flublok recipients and 4 Comparator recipients. One of the SAEs, vasovagal syncope following injection of Flublok, was considered related to administration of study vaccine.

Among 1078 adults 65 years of age and older (Studies 5 and 6 pooled), through up to 6 months post-vaccination, 4 deaths occurred, 2 in Flublok recipients and 2 in Comparator recipients. None were considered related to the study vaccines. SAEs were reported by 80 subjects (37 Flublok recipients, 43 Comparator recipients). None were considered related to the study vaccines.

Among 1314 adults 50 years of age and older (Study 7) for whom the incidence of rash, urticaria, swelling, non-pitting edema, or other potential hypersensitivity reactions were actively solicited for 30 days following vaccination, a total of 2.4% of Flublok recipients and 1.6% of Comparator recipients reported such events over the 30 day follow-up period. A total of 1.9% and 0.9% of Flublok and Comparator recipients, respectively, reported these events in the 7 days following vaccination. Of these solicited events, rash was most frequently reported (Flublok 1.3%, Comparator 0.8%) over the 30 day follow-up period.

6.2 Postmarketing Experience

The following events have been spontaneously reported during post-approval use of Flublok Quadrivalent. They are described because of the temporal relationship, the biologic plausibility of a causal relationship to Flublok Quadrivalent, and their potential seriousness. Because these events are reported voluntarily from a population of uncertain size, it is not always possible to reliably estimate their frequency or establish a causal relationship to vaccine exposure.

Immune system disorders: anaphylaxis, allergic reactions, and other forms of hypersensitivity (including urticaria).

7 DRUG INTERACTIONS

Data evaluating the concomitant administration of Flublok Quadrivalent with other vaccines are not available.

8 USE IN SPECIFIC POPULATIONS

8.1 Pregnancy

Pregnancy Exposure

Pregnancy outcomes in women who have been exposed to Flublok Quadrivalent during pregnancy are being monitored. Sanofi Pasteur Inc. is maintaining a prospective pregnancy exposure registry to collect data on pregnancy outcomes and newborn health status following vaccination with Flublok Quadrivalent during pregnancy. Healthcare providers are encouraged to enroll women who receive Flublok Quadrivalent during pregnancy in Sanofi Pasteur Inc.'s vaccination pregnancy registry by calling 1-800-822-2463.

Risk Summary

All pregnancies have a risk of birth defect, loss, or other adverse outcomes. In the U.S. general population, the estimated background risks of major birth defects and miscarriage in clinically recognized pregnancies are 2% to 4% and 15% to 20%, respectively. Available data on Flublok Quadrivalent and Flublok (trivalent formulation) administered to pregnant women are insufficient to inform vaccine-associated risks in pregnant women.

There were no developmental studies of Flublok Quadrivalent formulation performed in animals. The developmental effects of Flublok (trivalent formulation) are relevant to Flublok Quadrivalent because both vaccines are manufactured using the same process and have overlapping compositions. A developmental study of Flublok (trivalent formulation) has been performed in rats administered 0.5 mL divided of Flublok (trivalent formulation) prior to mating and during gestation. This study revealed no evidence of harm to the fetus due to Flublok (trivalent formulation) [see Data].

Clinical Considerations

Disease-associated Maternal and/or Embryo/Fetal Risk

Pregnant women are at increased risk of complications associated with influenza infection compared to non-pregnant women. Pregnant women with influenza may be at increased risk for adverse pregnancy outcomes, including preterm labor and delivery.

Data

Animal

In a developmental toxicity study, female rats were administered 0.5 mL divided of Flublok (trivalent formulation) by intramuscular injection twice prior to mating (35 days and 14 days prior to mating) and on gestation Day 6. No vaccine-related fetal malformations or variations and no adverse effects on pre-weaning development were observed in the study.

8.2 Lactation

Risk Summary

It is not known whether Flublok Quadrivalent is excreted in human milk. Data are not available to assess the effects of Flublok (trivalent formulation) or Flublok Quadrivalent on the breastfed infant or on milk production/excretion.

The developmental and health benefits of breastfeeding should be considered along with the mother's clinical need for Flublok Quadrivalent and any potential adverse effects on the breastfed child from Flublok Quadrivalent or from the underlying maternal condition. For preventive vaccines, the underlying condition is susceptibility to disease prevented by the vaccine.

8.4 Pediatric Use

Data from a randomized, controlled trial demonstrated that children 6 months to less than 3 years of age had diminished hemagglutinin inhibition (HI) responses to Flublok (trivalent formulation) as compared to a U.S.–licensed influenza vaccine approved for use in this population, strongly suggesting that Flublok (trivalent formulation) would not be effective in children younger than 3 years of age. Safety and effectiveness of Flublok Quadrivalent have not been established in children 3 years to less than 18 years of age.

8.5 Geriatric Use

Data from an efficacy study (Study 2), which included 1759 subjects ≥65 years and 525 subjects ≥75 years who received Flublok Quadrivalent, are insufficient to determine whether elderly subjects respond differently from younger subjects [see Clinical Trials Experience (6.1) and Clinical Studies (14)].

11 DESCRIPTION

Flublok Quadrivalent [Quadrivalent Influenza Vaccine] is a sterile, clear, colorless solution of recombinant hemagglutinin (HA) proteins from four influenza viruses for intramuscular injection. It contains purified HA proteins produced in a continuous insect cell line (expresSF+®) that is derived from Sf9 cells of the fall armyworm, Spodoptera frugiperda (which is related to moths, caterpillars and butterflies), and grown in serum-free medium composed of chemically-defined lipids, vitamins, amino acids, and mineral salts. Each of the four HAs is expressed in this cell line using a baculovirus vector (Autographa californica nuclear polyhedrosis virus), extracted from the cells with Triton X-100 and further purified by column chromatography. The purified HAs are then blended and filled into single-dose syringes.

Flublok Quadrivalent is standardized according to United States Public Health Service (USPHS) requirements. For the 2023-2024 influenza season it is formulated to contain 180 mcg HA per 0.5 mL dose, with 45 mcg HA of each of the following 4 influenza virus strains: A/West Virginia/30/2022 (A/Wisconsin/67/2022 pdm09-like virus) (H1N1), A/Darwin/6/2021 (H3N2), B/Austria/1359417/2021 and B/Phuket/3073/2013.

A single 0.5 mL dose of Flublok Quadrivalent contains sodium chloride (4.4 mg), monobasic sodium phosphate (0.2 mg), dibasic sodium phosphate (0.5 mg), and polysorbate 20 (Tween®20) (27.5 mcg). Each 0.5 mL dose of Flublok Quadrivalent may also contain residual amounts of baculovirus and Spodoptera frugiperda cell proteins (≤19 mcg), baculovirus and cellular DNA (≤10 ng), and Triton X-100 (≤100 mcg).

Flublok Quadrivalent contains no egg proteins, antibiotics, or preservatives. The single-dose, prefilled syringes contain no natural rubber latex.

12 CLINICAL PHARMACOLOGY

12.1 Mechanism of Action

Flublok Quadrivalent contains recombinant HA proteins of the four strains of influenza virus specified by health authorities for inclusion in the annual seasonal vaccine. These proteins function as antigens which induce a humoral immune response, measured by hemagglutination inhibition (HI) antibody.

Antibodies against one influenza virus type or subtype confer limited or no protection against another. Furthermore, antibodies to one antigenic variant of influenza virus might not protect against a new antigenic variant of the same type or subtype. Frequent (usually annual) development of antigenic variants through antigenic drift is the virologic basis for seasonal epidemics and the reason for the usual replacement of one or more influenza virus strains in each year's influenza vaccine. Therefore, influenza vaccines are standardized to contain the hemagglutinins of influenza virus strains (i.e., typically two type A and, in quadrivalent formulations, two type B), representing the influenza viruses likely to be circulating in the U.S. in the upcoming winter.

13 NONCLINICAL TOXICOLOGY

Flublok Quadrivalent has not been evaluated for carcinogenic or mutagenic potential, or for impairment of male fertility in animals. A developmental toxicity study conducted in rats vaccinated with Flublok (trivalent formulation) revealed no evidence of impaired female fertility [see Pregnancy (8.1)].

14 CLINICAL STUDIES

14.1 Efficacy against Laboratory-Confirmed Influenza

The efficacy of Flublok (trivalent formulation) is relevant to Flublok Quadrivalent because both vaccines are manufactured using the same process and have overlapping compositions [see Description (11)].

The efficacy of Flublok (trivalent formulation) in protecting against influenza illness was evaluated in a randomized, observer-blind, placebo-controlled multicenter trial conducted in the U.S. during the 2007-2008 influenza season in adults 18-49 years of age (Study 3).

Study 3 enrolled and vaccinated 4648 healthy adults (mean age 32.5 years) randomized in a 1:1 ratio to receive a single dose of Flublok (n=2344) or saline placebo (n=2304). Among enrolled subjects, 59% were female, 67% were white, 19% African-American, 2% Asian, <1% other races, and 11% of Latino/Hispanic ethnicity. Culture-confirmed influenza was assessed by active and passive surveillance for influenza-like illness (ILI) beginning 2 weeks post-vaccination until the end of the influenza season, approximately 7 months post-vaccination. ILI was defined as having at least 2 of 3 symptoms (no specified duration) in the following categories: 1) fever ≥100ºF; 2) respiratory symptoms (cough, sore throat, or runny nose/stuffy nose); or 3) systemic symptoms (myalgias, arthralgias, headache, chills/sweats, or tiredness/malaise). For subjects with an episode of ILI, nasal and throat swab samples were collected for viral culture.

The primary efficacy endpoint of Study 3 was Centers for Disease Control-defined influenza-like illness (CDC-ILI) with a positive culture for an influenza virus strain antigenically resembling a strain represented in Flublok. CDC-ILI is defined as fever of ≥100°F oral accompanied by cough, sore throat, or both on the same day or on consecutive days. Attack rates and vaccine efficacy (VE), defined as the reduction in the influenza rate for Flublok relative to placebo, were calculated for the total vaccinated cohort (n=4648).

The pre-defined success criterion for the primary efficacy analysis was that the lower bound of the 95% confidence interval (CI) of VE should be at least 40%. Vaccine efficacy against antigenically matched culture-confirmed CDC-ILI could not be determined reliably because 96% of the influenza isolates obtained from subjects in Study 3 were not antigenically matched to the strains represented in the vaccine. An exploratory analysis of VE of Flublok against all strains, regardless of antigenic match, isolated from any subject with an ILI, not necessarily meeting CDC- ILI criteria, demonstrated an efficacy estimate of 44.8% (95% CI 24.4, 60.0). See Table 3 for a presentation of VE by case definition and antigenic similarity.

Table 3: Vaccine Efficacy against Culture-Confirmed Influenza in Healthy Adults 18-49 Years of Age, Study 3 [In Study 3 (NCT00539981) vaccine efficacy analyses were conducted on the Total Vaccinated Cohort (all randomized subjects who received study vaccine according to the treatment actually received and who provided data). Vaccine efficacy (VE) = 1 minus the ratio of Flublok/placebo infection rates.]
Case definition | Flublok (trivalent) (N=2344) |  | Saline Placebo (N=2304) |  | Flublok Vaccine Efficacy [Determined under the assumption of Poisson event rates, according to Breslow and Day, 1987.] , % | 95% Confidence Interval
Case definition | Cases, n | Rate, % | Cases, n | Rate, % | Flublok Vaccine Efficacy [Determined under the assumption of Poisson event rates, according to Breslow and Day, 1987.] , % | 95% Confidence Interval
Positive culture with a strain represented in the vaccine
CDC-ILI, all matched strains [Meets CDC influenza-like illness (CDC-ILI) defined as fever of ≥100°F oral accompanied by cough and/or sore throat, on the same day or on consecutive days.] , [Primary endpoint of trial.] | 1 | 0.04 | 4 | 0.2 | 75.4 | (-148.0, 99.5)
Any ILI, all matched strains [All culture-confirmed cases are considered, regardless of whether they qualified as CDC-ILI.] , [Secondary endpoint of trial.] | 2 | 0.1 | 6 | 0.3 | 67.2 | (-83.2, 96.8)
Positive culture with any strain, regardless of match to the vaccine
CDC-ILI, all strains, [Exploratory (prespecified) endpoint of trial.] | 44 | 1.9 | 78 | 3.4 | 44.6 | (18.8, 62.6)
Sub-Type A | 26 | 1.1 | 56 | 2.4 | 54.4 | (26.1, 72.5)
Type B | 18 | 0.8 | 23 | 1.0 | 23.1 | (-49.0, 60.9)
Any ILI, all strains | 64 | 2.7 | 114 | 4.9 | 44.8 | (24.4, 60.0)
Sub-Type A | 41 | 1.7 | 79 | 3.4 | 49.0 | (24.7, 65.9)
Type B | 23 | 1.0 | 36 | 1.6 | 37.2 | (-8.9, 64.5)

Study 2 evaluated the efficacy of Flublok Quadrivalent in a randomized, observer-blind, active-controlled, multicenter trial conducted during the 2014-2015 influenza season in adults 50 years of age and older. A total of 8963 healthy, medically stable adults (mean age 62.5 years) were randomized in a 1:1 ratio to receive a single dose of Flublok Quadrivalent (n=4474) or a U.S.–licensed quadrivalent inactivated influenza vaccine (Comparator, Fluarix Quadrivalent, manufactured by Glaxo SmithKline) (n=4489). Among randomized subjects, 58% were female, 80% white, 18% black/African-American, 2% other races, and 5% of Hispanic/Latino ethnicity. A total of 5186 (60%) subjects were 50-64 years of age and 3486 (40%) were ≥65 years of age. Real-time polymerase chain reaction (rtPCR)–confirmed influenza was assessed by active and passive surveillance for influenza-like illness (ILI) beginning 2 weeks post-vaccination until the end of the influenza season, approximately 6 months post-vaccination. ILI was defined as having at least one symptom (no specified duration) in each of two categories of respiratory and systemic symptoms. Respiratory symptoms included sore throat, cough, sputum production, wheezing and difficulty breathing. Systemic symptoms included fever >99°F (>37°C) oral, chills, fatigue, headache and myalgia. For subjects with an episode of ILI, a nasopharyngeal swab sample was collected for rtPCR testing and reflex viral culture of rtPCR-positive samples.

The primary efficacy endpoint of Study 2 was rtPCR-positive, protocol-defined ILI due to any strain of influenza. Attack rates and relative vaccine efficacy (rVE), defined as 1 – (Attack rate Flublok Quadrivalent/ Attack Rate Comparator), were calculated for the total efficacy population (n=8604) for the primary efficacy endpoint and for several alternative efficacy endpoints (Table 4). Antigenic and phylogenetic evaluations of the similarity ("matching") of clinical isolates to vaccine antigens were not performed. CDC epidemiological data for the 2014-2015 influenza season indicated that Influenza A (H3N2) viruses predominated and that most influenza A/H3N2 viruses were antigenically dissimilar while A/H1N1 and B viruses were antigenically similar to vaccine antigens.

Table 4: Relative Vaccine Efficacy (rVE) of Flublok Quadrivalent versus Comparator against Laboratory-Confirmed Influenza, Regardless of Antigenic Similarity to Vaccine Antigens, Adults 50 Years of Age and Older, Study 2 (Efficacy Population) [Study 2 is registered as NCT02285998.] , [Efficacy Population included all randomized subjects who received study vaccine and provided any follow-up documentation for influenza-like illness beginning at least 14 days post vaccination. Excluded subjects with protocol deviations that could adversely affect efficacy.]
 | Flublok Quadrivalent (N=4303) |  | Comparator (N=4301) |  |  | rVE % (95% CI)
 | n | Attack Rate % (n/N) | n | Attack Rate % (n/N) | RR | rVE % (95% CI)
All rtPCR-positive Influenza [Primary Analysis. All cases of rtPCR-confirmed influenza are included. Antigenic characterization and genetic sequencing to determine similarity of isolates to vaccine antigens were not performed. CDC surveillance data indicated that the majority of influenza A/H3N2 wild type viruses were antigenically distinct whereas influenza A/H1N1 and type B viruses were antigenically similar to vaccine antigens during the 2014-2015 season. Study 2 met the pre-specified success criterion for the primary endpoint (lower limit of the 2-sided 95% CI of vaccine efficacy for Flublok Quadrivalent relative to Comparator should be not less than -20%).] | 96 | 2.2 | 138 | 3.2 | 0.70 | 30 (10, 47)
All rtPCR-positive Influenza A [Post hoc analyses. All cases of influenza A were A/H3N2. Cases of influenza B were not distinguished by lineage.] | 73 | 1.7 | 114 | 2.7 | 0.64 | 36 (14, 53)
All rtPCR-positive Influenza B | 23 | 0.5 | 24 | 0.6 | 0.96 | 4 (-72, 46)
All Culture-confirmed Protocol-defined ILI, [Culture of rtPCR-positive samples was performed in MDCK cells.] | 58 | 1.3 | 101 | 2.3 | 0.57 | 43 (21, 59)
Abbreviations: rtPCR=reverse transcriptase polymerase chain reaction; Comparator=U.S.–licensed quadrivalent inactivated influenza vaccine, Fluarix Quadrivalent, manufactured by GlaxoSmithKline; n=number of influenza cases; N=number of subjects in treatment group; RR=relative risk (Attack Rate Flublok/Attack Rate IIV4); rVE = ([1-RR] × 100).

14.2 Immunogenicity of Flublok Quadrivalent

Study 1 evaluated the immunogenicity of Flublok Quadrivalent as compared to a U.S.–licensed quadrivalent inactivated influenza vaccine (Comparator) (Fluarix Quadrivalent, manufactured by GlaxoSmithKline) in a randomized, observer-blind, active-controlled, multicenter trial conducted during the 2014-2015 influenza season in healthy adults 18-49 years of age. A total of 1350 subjects were enrolled, randomized 3:1, and vaccinated with Flublok Quadrivalent (998 subjects) or Comparator (332 subjects). Subjects were predominantly female (65%), white (60%), black/African American (37%), and of non-Hispanic/Latino ethnicity (84%), with a mean age of 33.5 years. Of the total vaccinated population, 1292 subjects (969 Flublok Quadrivalent and 323 IIV4 recipients, respectively) were evaluable for immune responses (Immunogenicity Population).

Post-vaccination immunogenicity was evaluated on sera obtained 28 days after administration of a single dose of study vaccine. Hemagglutination inhibition (HI) geometric mean titers (GMTs) were determined for the two vaccine groups for each vaccine antigen. Immunogenicity was compared by calculating the difference in seroconversion rates (SCR) and the ratios of GMTs of Comparator to Flublok Quadrivalent. Seroconversion was defined as either a pre-vaccination HI titer of <1:10 and a postvaccination HI titer of ≥1:40, or a pre-vaccination HI titer of ≥1:10 and a minimum 4-fold rise in postvaccination HI titer, at Day 28.

Study 1 had eight co-primary endpoints: Day 28 HI seroconversion rates and GMTs for each of the four antigens contained in the study vaccines. GMTs were compared based on the upper bound of the two-sided 95% CI of the GMT ratio of Comparator to Flublok Quadrivalent. Success in meeting this endpoint was pre-defined as an upper bound (UB) of the two-sided 95% CI of GMTComparator / GMTFlublok Quadrivalent ≤1.5. Flublok Quadrivalent met the success criterion for GMTs for three of the four antigens but not for the B/Victoria lineage antigen (Table 5).

Table 5: Comparison of Day 28 Post-Vaccination Geometric Mean Titers (GMT) for Flublok Quadrivalent and Comparator in Adults 18-49 Years of Age, Study 1 (Immunogenicity Population) [Study 1 is registered as NCT02290509.] , [The Immunogenicity Population included all randomized subjects who received a dose of study vaccine, provided serum samples for Day 0 and Day 28 within specified windows, and had no major protocol deviations that might adversely affect the immune response. The pre-defined success criterion for the GMT ratio of Comparator to Flublok Quadrivalent was that the upper bound of the 2-sided 95% CI of the GMT ratio, GMT Comparator / GMT Flublok Quadrivalent at 28 days post-vaccination, must not exceed 1.5.] , [HI titers were assayed using egg-derived antigens.] , [Comparator: U.S.–licensed quadrivalent inactivated influenza vaccine, Fluarix Quadrivalent, manufactured by GlaxoSmithKline.]
Antigen | Post-vaccination GMT Flublok Quadrivalent N=969 | Post-vaccination GMT Comparator N=323 | GMT Ratio Comparator/Flublok Quadrivalent [95% CI]
A/H1N1 | 493 | 397 | 0.81 (0.71, 0.92)
A/H3N2 | 748 | 377 | 0.50 (0.44, 0.57)
B/Yamagata | 156 | 134 | 0.86 (0.74, 0.99)
B/Victoria | 43 | 64 | 1.49 (1.29, 1.71)
Abbreviations: CI, confidence interval; GMT, geometric mean titer.

Success in meeting the seroconversion rate (SCR) endpoint was pre-defined as an upper bound (UB) of the two-sided 95% CI of SCR Comparator – SCR Flublok Quadrivalent ≤10%. Flublok Quadrivalent met the success criterion for SCRs for three of the four antigens but not for the B/Victoria lineage antigen (Table 6). Sub-population analyses of immunogenicity did not reveal significant differences between genders. Sub-analyses according to race and ethnicity were not informative because the sizes of the subsets were insufficient to reach meaningful conclusions. The HI response to the B/Victoria lineage antigen was low in both vaccine groups.

Table 6: Comparison of Day 28 Seroconversion Rates for Flublok Quadrivalent and Comparator in Adults 18-49 Years of Age, Study 1 (Immunogenicity Population) [Study 1 is registered as NCT02290509.] , [The Immunogenicity Population included all randomized subjects who received a dose of study vaccine, provided serum samples for Day 0 and Day 28 within specified windows, and had no major protocol deviations that might adversely affect the immune response. The pre-defined success criterion for the SCR difference between Comparator and Flublok Quadrivalent was that the upper bound of the 2-sided 95% CI of the SCR difference IIV4 – Flublok Quadrivalent at 28 days post-vaccination, must not exceed 10%.] , [HI titers were assayed using egg-derived antigens.] , [Comparator was a U.S.–licensed quadrivalent inactivated influenza vaccine, Fluarix Quadrivalent, manufactured by GlaxoSmithKline.]
Antigen | SCR (%, 95% CI) Flublok Quadrivalent N=969 | SCR (%, 95% CI) Comparator N=323 | SCR Difference (%) Comparator - Flublok Quadrivalent [95% CI]
A/H1N1 | 66.7 (63.6, 69.6) | 63.5 (58.0, 68.7) | -3.2 (-9.2, 2.8)
A/H3N2 | 72.1 (69.2, 74.9) | 57.0 (51.4, 62.4) | -15.2 (-21.3, -9.1)
B/Yamagata | 59.6 (56.5, 62.8) | 60.4 (54.8, 65.7) | 0.7 (-5.4, 6.9)
B/Victoria | 40.6 (37.4, 43.7) | 58.2 (52.6, 63.6) | 17.6 (11.4, 23.9)
Abbreviations: CI, confidence interval; SCR, seroconversion rate
Seroconversion was defined as a pre-vaccination HI titer <1:10 and a post-vaccination HI titer ≥1:40 or a pre-vaccination HI titer ≥1:10 and a minimum four-fold rise in post-vaccination HI antibody titer.

16 HOW SUPPLIED/STORAGE AND HANDLING

16.1 How Supplied

Flublok Quadrivalent is supplied as a single-dose, 0.5 mL syringe in a 10 syringe carton:

Presentation | Carton NDC Number | Components and NDC Number
Single-Dose Prefilled Syringe | 49281-723-10 | Ten 0.5 mL single-dose prefilled syringes [NDC 49281-723-88]

16.2 Storage and Handling

- Store refrigerated between 2°C and 8°C (36°F and 46°F).
- Do not freeze. Discard if product has been frozen.
- Protect syringes from light.
- Do not use after expiration date shown on the label.

17 PATIENT COUNSELING INFORMATION

Inform the vaccine recipient of the potential benefits and risks of vaccination with Flublok Quadrivalent.

Inform the vaccine recipient that:

- Flublok Quadrivalent contains non-infectious proteins that cannot cause influenza.
- Flublok Quadrivalent stimulates the immune system to produce antibodies that help protect against the influenza viruses carrying the proteins contained in the vaccine, but does not prevent other respiratory infections.

Instruct the vaccine recipient to report any adverse events to their healthcare provider and/or to the Vaccine Adverse Event Reporting System (VAERS).

Provide the vaccine recipient with the Vaccine Information Statements which are required by the National Childhood Vaccine Injury Act of 1986 to be given prior to vaccination. These materials are available free of charge at the Centers for Disease Control (CDC) website (www.cdc.gov/vaccines).

Encourage women who receive Flublok or Flublok Quadrivalent while pregnant to notify Sanofi Pasteur Inc. by calling 1-800-822-2463.

Instruct the vaccine recipient that annual vaccination to prevent influenza is recommended.

Manufactured by Protein Sciences Corporation (Meriden, CT).

U.S. license No. 1795.

Distributed by Sanofi Pasteur Inc.

Flublok is a registered trademark of Protein Sciences Corporation.

PRINCIPAL DISPLAY PANEL - 0.5 mL Syringe Label - 7915

NDC 49281-722-88

Influenza Vaccine
FLUBLOK® Quadrivalent
2022/2023 Formula
No Preservative

Single-Dose (0.5 mL)
Rx only
For Intramuscular Injection
Mfd by: Protein Sciences Corp.

PRINCIPAL DISPLAY PANEL - 0.5 mL Syringe Carton - 7916

NDC 49281-722-10

Influenza Vaccine
FLUBLOK® Quadrivalent
2022 / 2023 Formula

10 Single-Dose
Prefilled Syringes
0.5 mL each

Rx only

For 18 Years of Age and Older

For Intramuscular Administration Only

SANOFI PASTEUR

PRINCIPAL DISPLAY PANEL - 0.5 mL Syringe Label - CP-1931

NDC 49281-722-88

Influenza Vaccine
FLUBLOK® Quadrivalent
2022/2023 Formula
No Preservative

Single-Dose (0.5 mL)
Rx only
For Intramuscular Injection
Mfd by: Protein Sciences Corp.

CP-1931

PRINCIPAL DISPLAY PANEL - 0.5 mL Syringe Carton - CP-1930

NDC 49281-722-10

Influenza Vaccine
FLUBLOK® Quadrivalent

2022 / 2023 Formula

10 Single-Dose
Prefilled Syringes
0.5 mL each

Rx only

For 18 Years of Age and Older

For Intramuscular Administration Only

SANOFI PASTEUR

PRINCIPAL DISPLAY PANEL - 0.5 mL Syringe Label - 884931

NDC 49281-723-88

Influenza Vaccine
FLUBLOK® Quadrivalent
2023/2024 Formula
No Preservative

Single-Dose (0.5 mL)
Rx only
For Intramuscular Injection
Mfd by: Protein Sciences Corp.

PRINCIPAL DISPLAY PANEL - 0.5 mL Syringe Carton - 884932

NDC 49281-723-10

Influenza Vaccine
FLUBLOK® Quadrivalent

2023 / 2024 Formula

10 Single-Dose
Prefilled Syringes
0.5 mL each

Rx only

For 18 Years of Age and Older

For Intramuscular Administration Only

SANOFI PASTEUR

PRINCIPAL DISPLAY PANEL - 0.5 mL Syringe Label - CP-1941

NDC 49281-723-88

Influenza Vaccine
FLUBLOK® Quadrivalent
2023/2024 Formula
No Preservative

Single-Dose (0.5 mL)
Rx only
For Intramuscular Injection
Mfd by: Protein Sciences Corp.

CP-1941

PRINCIPAL DISPLAY PANEL - 0.5 mL Syringe Carton - CP-1940

NDC 49281-723-10

Influenza Vaccine
FLUBLOK® Quadrivalent

2023 / 2024 Formula

10 Single-Dose
Prefilled Syringes
0.5 mL each

Rx only

For 18 Years of Age and Older

For Intramuscular Administration Only

SANOFI PASTEUR